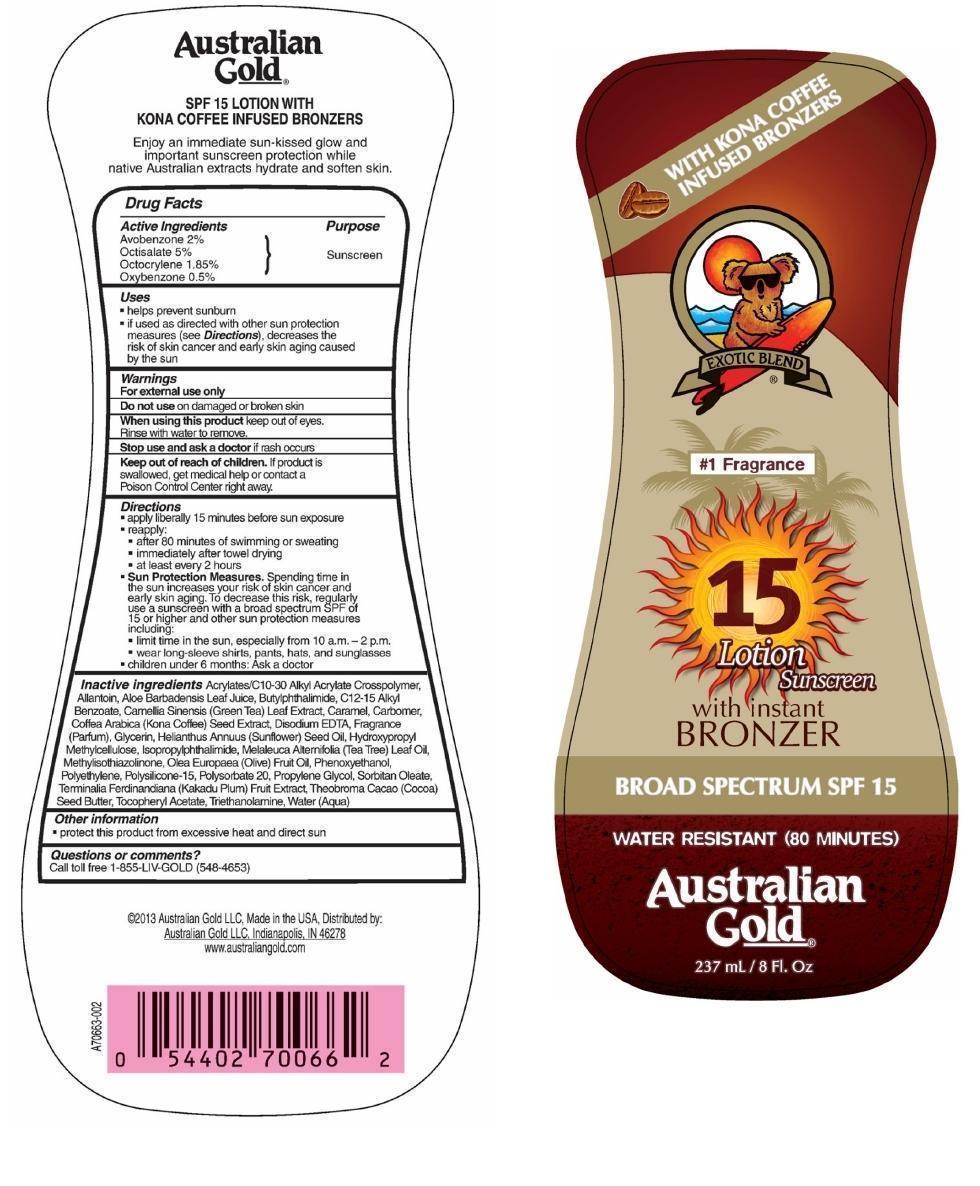 DRUG LABEL: Australian Gold
NDC: 58443-0038 | Form: LOTION
Manufacturer: Prime Enterprises, Inc.
Category: otc | Type: HUMAN OTC DRUG LABEL
Date: 20200117

ACTIVE INGREDIENTS: AVOBENZONE 19.6 mg/1 mL; OCTISALATE 49 mg/1 mL; OCTOCRYLENE 18.13 1/1 mL; OXYBENZONE 4.9 mg/1 mL
INACTIVE INGREDIENTS: CARBOMER COPOLYMER TYPE A; ALLANTOIN; ALOE VERA LEAF; N-BUTYLPHTHALIMIDE; ISOPROPYLPHTHALIMIDE; ALKYL (C12-15) BENZOATE; CARAMEL; CARBOMER HOMOPOLYMER TYPE C (ALLYL PENTAERYTHRITOL CROSSLINKED); EDETATE DISODIUM; SUNFLOWER OIL; HYPROMELLOSES; TEA TREE OIL; HIGH DENSITY POLYETHYLENE; POLYSORBATE 20; COCOA BUTTER; OLIVE OIL; OLETH-10; PHENOXYETHANOL; PROPYLENE GLYCOL; SORBITAN MONOOLEATE; .ALPHA.-TOCOPHEROL ACETATE; TROLAMINE; METHYLISOTHIAZOLINONE; POLYSILICONE-15; WATER; GLYCERIN; ARABICA COFFEE BEAN; GREEN TEA LEAF; KAKADU PLUM

Active ingredients

Avobenzone 2 %, Octisalate 5 %, Octocrylene 1.85 %, and Oxybenzone 0.5 %

Purpose

Sunscreen

Uses

- helps prevent sunburn
- if used as directed with other sun protection measures (see Directions), decreases the risk of skin cancer and early skin aging caused by the sun

Warnings

OTHER SAFETY INFORMATION

For external use only

Do not use on damaged or broken skin.

When using this product keep out of eyes. Rinse with water to remove.

Stop use and ask a doctor if rash occurs.

Keep out of reach of children. If product is swallowed, get medical help or contact a Poison Control Center right away.

Directions

- apply liberally 15 minutes before sun exposure
- reapply:
  - after 80 minutes of swimming or sweating
  - immediately after towel drying
  - at least every 2 hours
- Sun Protection Measures.Spending time in the sun increases your risk of skin cancer and early skin aging. To decrease this risk, regularly use a sunscreen with a broad spectrum SPF of 15 or higher and other sun protection measures including:
  - limit time in the sun, especially from 10 a.m. – 2 p.m.
  - wear long-sleeve shirts, pants, hats, and sunglasses
- Children under 6 months: Ask a doctor

Inactive Ingredients

Acrylates/C10-30 Alkyl Acrylate Crosspolymer, Allantoin, Aloe Barbadensis Leaf Juice, Butylphthalimide, C12-15 Alkyl Benzoate, Camellia Sinensis (Green Tea) Leaf Extract, Caramel, Carbomer, Coffea Arabica (Kona Coffee) Seed Extract, Disodium EDTA, Fragrance (Parfum), Glycerin, Helianthus Annuus (Sunflower) Seed Oil, Hydroxypropyl Methylcellulose, Isopropylphthalimide, Melaleuca Alternifolia (Tea Tree) Leaf Oil, Methylisothiazolinone, Olea Europaea (Olive) Fruit Oil, Phenoxyethanol, Polyethylene, Polysilicone-15, Polysorbate 20, Propylene Glycol, Sorbitan Oleate, Terminalia Ferdinandiana (Kakadu Plum) Fruit Extract, Theobroma Cacao (Cocoa) Seed Butter, Tocopheryl Acetate, Triethanolamine, Water (Aqua)

Other information

- protect this product from excesive heat and direct sun

Questions or Comments?

Call toll free 1-855-LIV-GOLD (548-4653)

PRINCIPAL DISPLAY PANEL - 237 mL Bottle Label

WITH KONA COFFEE

INFUSED BRONZERS

EXOTIC BLEND

#1 Fragrance

15

Lotion

Sunscreen

with instant

BRONZER

BROAD SPECTRUM SPF 15

WATER RESISTANT (80 MINUTES)

Australian

G old®

237 mL / 8 FL. Oz